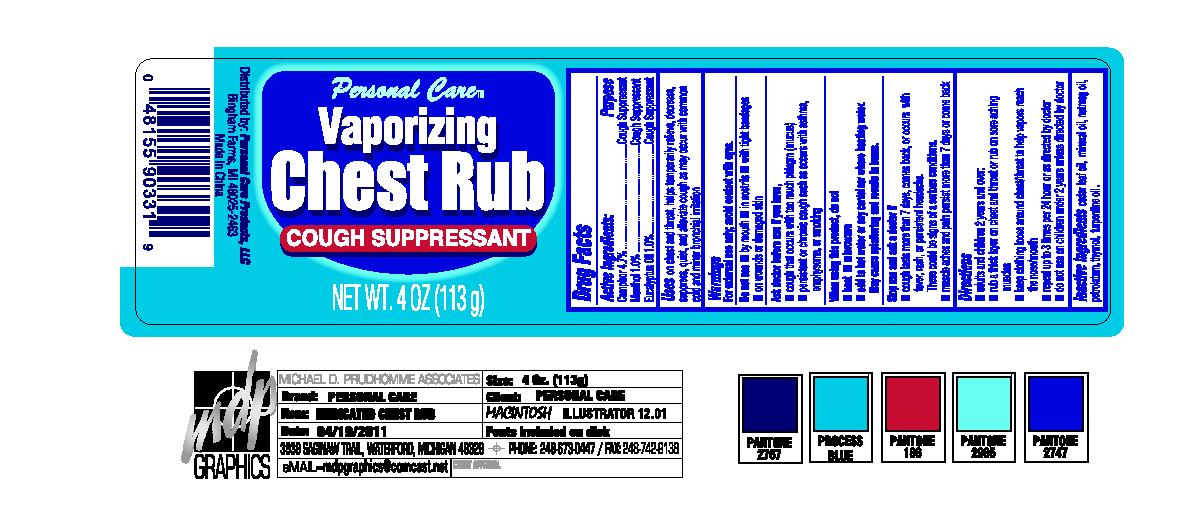 DRUG LABEL: Vaporizing Chest
                        
NDC: 29500-9033 | Form: SALVE
Manufacturer: Personal Care Products
Category: otc | Type: HUMAN OTC DRUG LABEL
Date: 20111121

ACTIVE INGREDIENTS: CAMPHOR (SYNTHETIC) 5.31 g/113 g; MENTHOL 1.13 g/113 g; EUCALYPTUS OIL 1.13 g/113 g
INACTIVE INGREDIENTS: CEDAR LEAF OIL; MINERAL OIL; NUTMEG OIL; PETROLATUM; THYMOL; TURPENTINE

Vaporizing Chest

Active Ingredients

Camphor 4.7%

Menthol 1.0%

Eucalyptus Oil 1.0%

Purpose Cough Suppressant

Do not use on children under 2 years unless directed by doctor

Directions

adults and children 2 years and over;

rub a thick layer on chest and throat or rub on sore aching muscles;

keep clothing loose around chest/throat to help vapors reach the nose/mouth;

repeat up to 3 times per 24 hours or as directed by doctor;

do not use on children under 2 years unless directed by doctor

Inactive ingredients

cedar leaf oil, mineral oil, nutmeg oil, petrolatum, thymol, turpentine oil.

Warnings

For external use only, avoid contact with eyes.

Do not use by mouth, in nostrils, with tight bandages, on wounds or damaged skin

Ask doctor before use if you have,

cough that occurs with too much phlegm (mucus

persistent or chronic cough such as occurs with asthma, emphysema, or smoking

When using this product, do not
heat
microwave
add to hot water or any container where heating water. May cause splattering and results in burns.
Stop use and ask a doctor if
cough lasts more than 7 days comes back, or occurs with fever, rash or persistent headache.
These could be signs of a serious conditions.
muscle aches and pain persist more than 7 days or come back.

INDICATIONS AND USAGE

Uses on chest and throat, helps temporarily relieve, decrease, suppress, quiet and alleviate cough as may occur with common cold and minor bronchial irritation.

PACKAGE LABEL

Personal Care

Vaporizing Chest Rub Cough Suppressant

Net Wt. 4 oz (113 g)